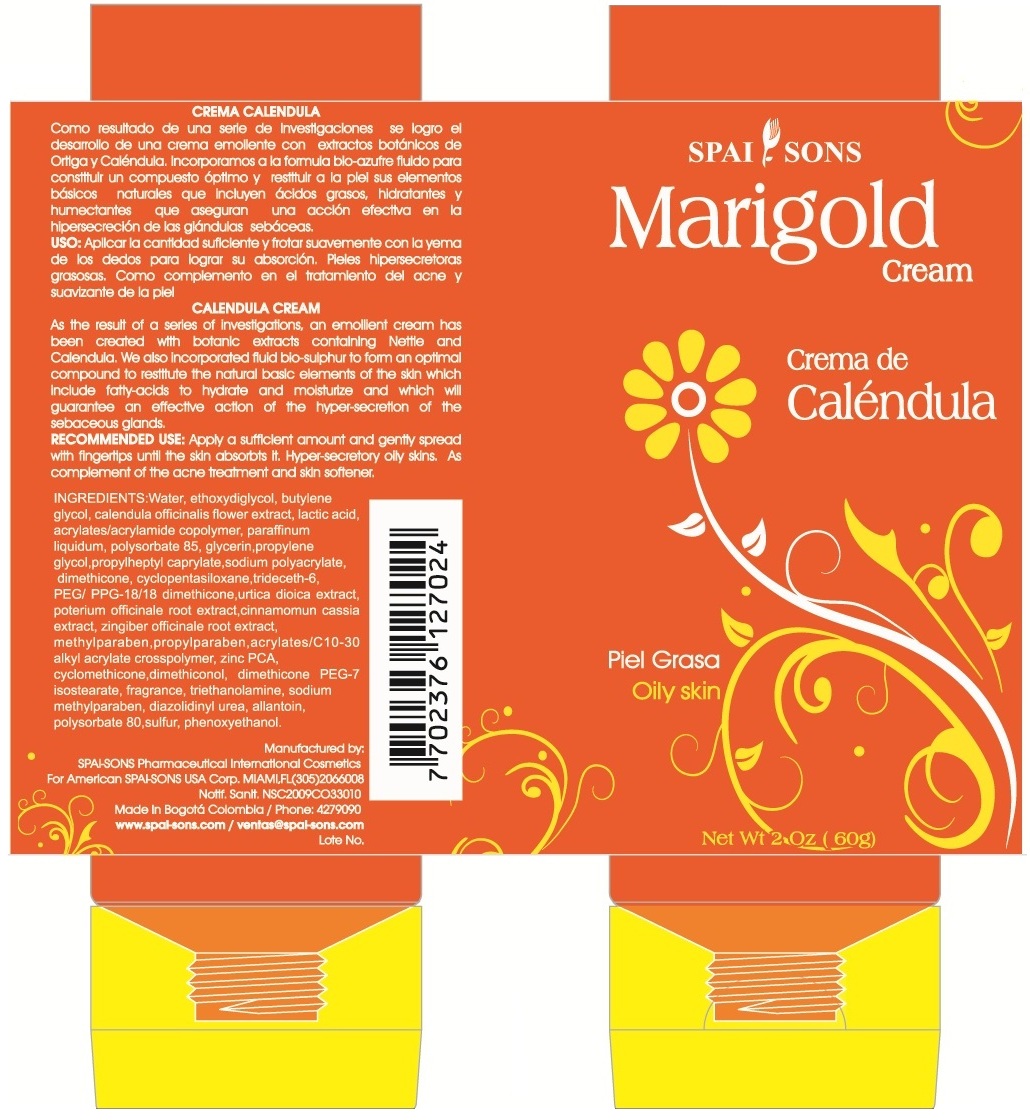 DRUG LABEL: SPAI-SONS 
NDC: 66854-023 | Form: CREAM
Manufacturer: SPAI-SONS PHARMACEUTICAL INTERNATIONAL COSMETICS
Category: otc | Type: HUMAN OTC DRUG LABEL
Date: 20120607

ACTIVE INGREDIENTS: SULFUR 0.1 g/100 g
INACTIVE INGREDIENTS: WATER; DIETHYLENE GLYCOL MONOETHYL ETHER; PROPYLENE GLYCOL; BUTYLENE GLYCOL; CALENDULA OFFICINALIS FLOWER; LACTIC ACID; MINERAL OIL; POLYSORBATE 85; GLYCERIN; PROPYLHEPTYL CAPRYLATE; SODIUM POLYACRYLATE (8000 MW); DIMETHICONE; CYCLOMETHICONE 5; TRIDECETH-6; PEG/PPG-18/18 DIMETHICONE; URTICA DIOICA LEAF; SANGUISORBA OFFICINALIS ROOT; CHINESE CINNAMON; GINGER; CARBOMER COPOLYMER TYPE B (ALLYL PENTAERYTHRITOL CROSSLINKED); ZINC PIDOLATE; CYCLOMETHICONE; DIMETHICONOL (41 MPA.S); DIMETHICONE PEG-7 ISOSTEARATE; TROLAMINE; METHYLPARABEN SODIUM; DIAZOLIDINYL UREA; ALLANTOIN; POLYSORBATE 80; PHENOXYETHANOL

SPAI-SONS CREMA DE CALENDULA PIEL GRASA/ MARIGOLD CREAM OILY SKIN

ACTIVE INGREDIENT

Marigold extracts of medicinal plants, bio-sulfur and a selection of natural assets for the treatment of some skin rashes.

PURPOSE

For treatment of some skin rashes that do not participate in the pathogenic microorganisms, particularly the treatment of acne.

Keep out of reach of children

INDICATIONS AND USAGE

Due to its composition Marigold cream is very active to normalize oily skin, hyper-secretory, body rashes, burns, or as an accelerator of wound healing, its greatest virtue is the design as an adjunct in the treatment of acne.

WARNINGS

Avoid the contact with eyes. suspend its use if you notice an unfavorable reaction on the skin.

DOSAGE AND ADMINISTRATION

Apply a sufficient amount and gently spread with fingertips until the skin absorbs it. This product is for topical application

INACTIVE INGREDIENT

The formula includes extracts of medicinal plants and bio-sulfur, a trace element essential to cellular organization, is an asset which splits fats and regulates the secretion of the sebaceous glands, act synergistically other extracts such as healing, anti-inflamatory, antiseptic, antipuritic dermal, refreshing and soothing.

IMAGE OF THE LABEL